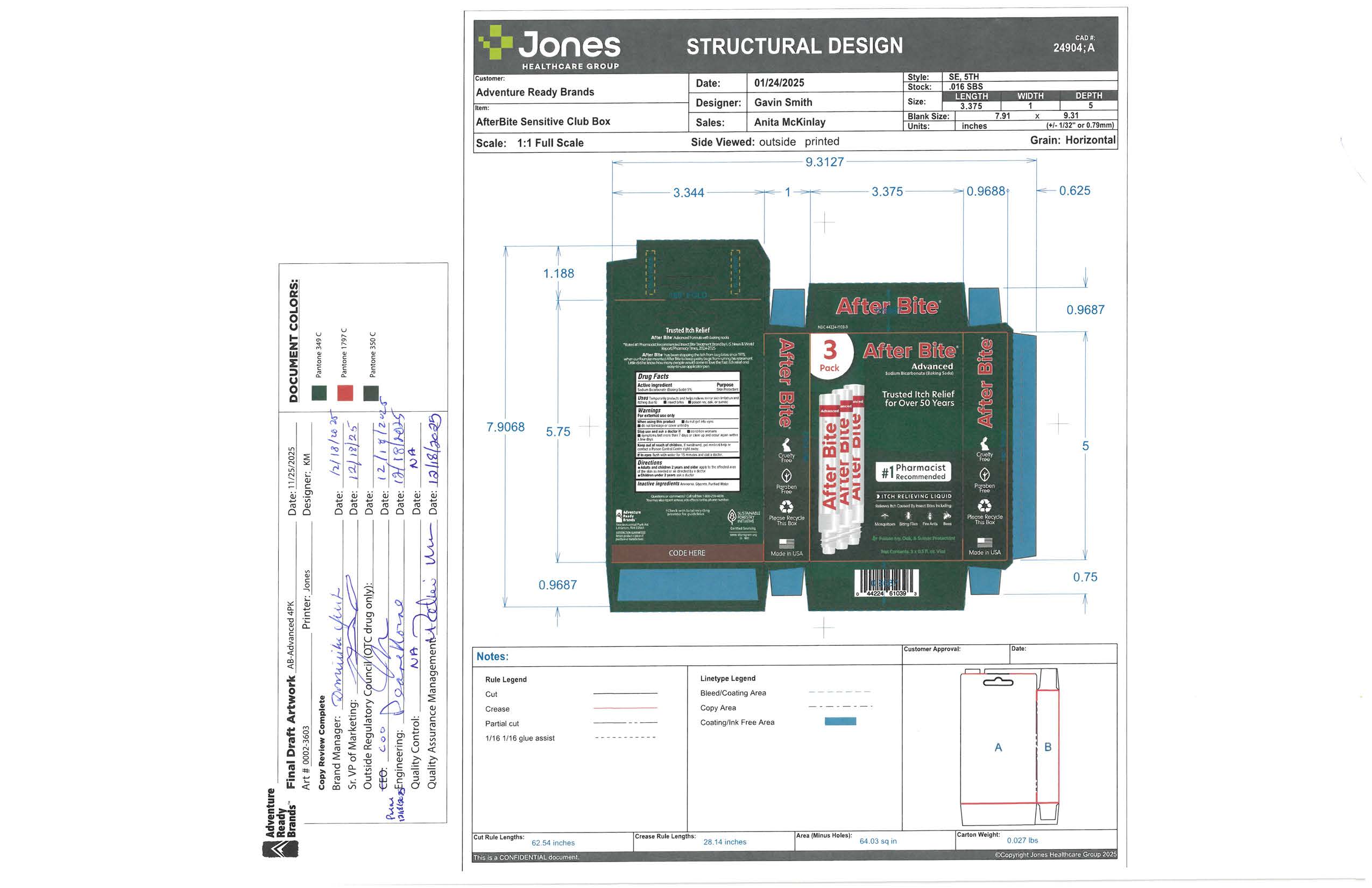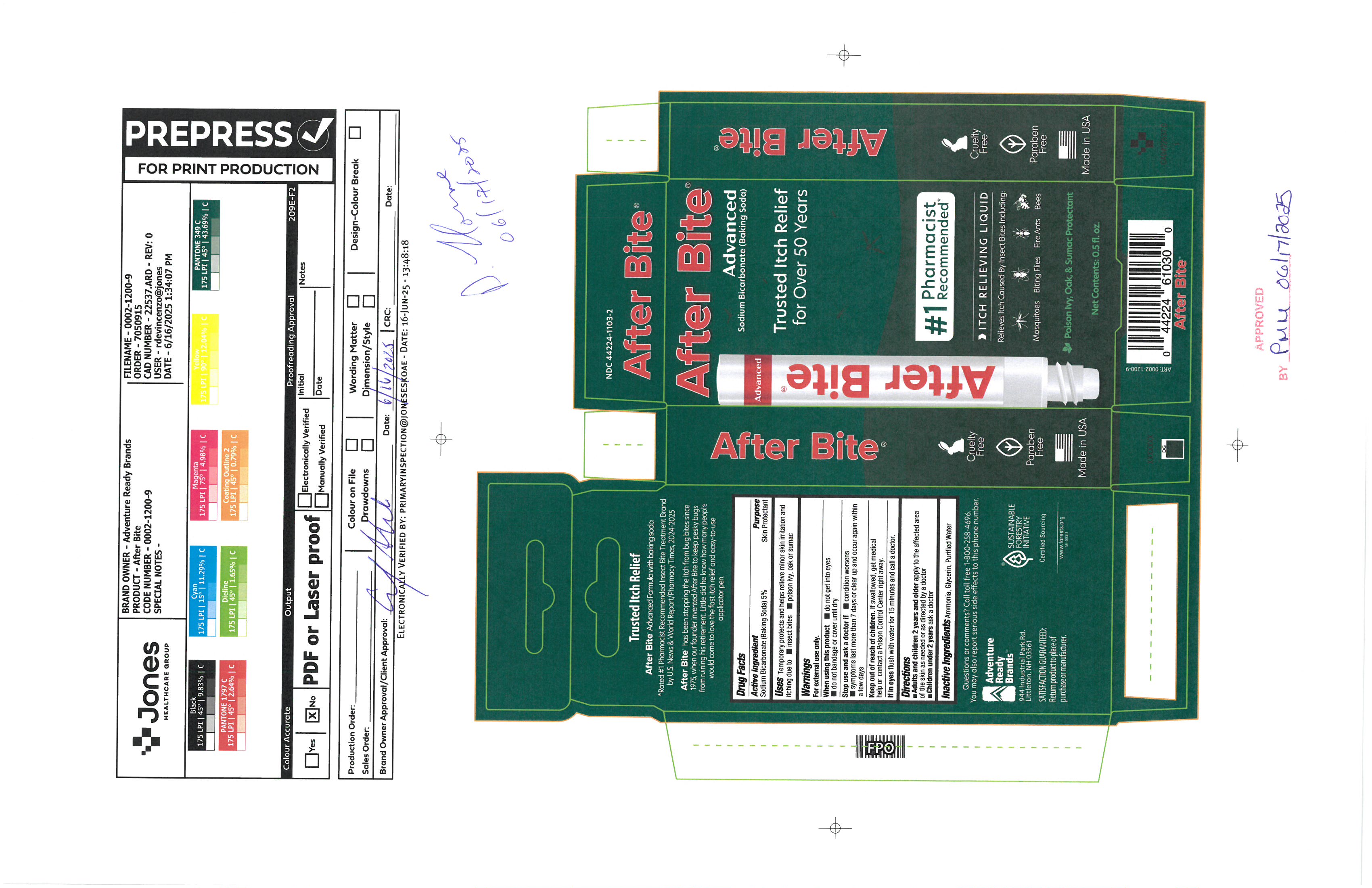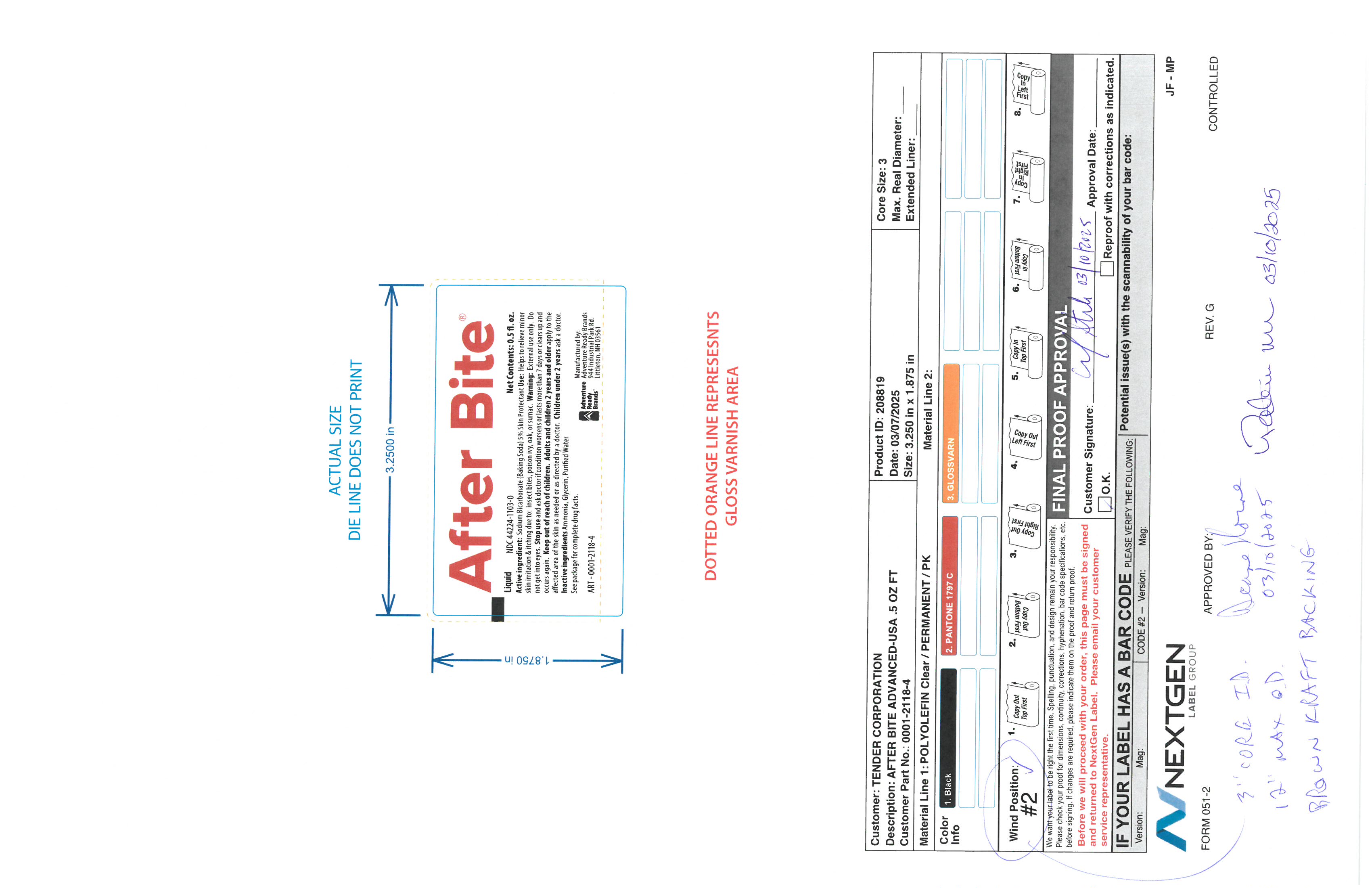 DRUG LABEL: After Bite Advanced
NDC: 44224-1103 | Form: LIQUID
Manufacturer: Tender Corporation d/b/a Adventure Ready Brands
Category: otc | Type: HUMAN OTC DRUG LABEL
Date: 20251218

ACTIVE INGREDIENTS: SODIUM BICARBONATE 0.7 g/14 g
INACTIVE INGREDIENTS: GLYCERIN 0.14 g/14 g; AMMONIA 0.778 g/14 g; WATER 12.376 g/14 g

After Bite Advanced

Active Ingredient / Purpose

Sodium Bicarbonate (Baking Soda) 5% Skin Protectant

Uses

Temproarily protects and helps relieve minor skin irritation and itching due to insect bite poison ivy, oak sumac

Warnings

For external use only.

if in eyes

flush with water for 15 minutes call a doctor

When using this product

do not get into eyes, do not bandage or cover until dry

Stop use and ask a doctor if

condition worsens , symptoms last more than 7 days or clear up and oiccur again within a few days

Keep out of reach of children

if swollowed, get medical help or contact poisin control center right away.

Directions

Adults and children 2 years and older apply to the affected area of the skin as needed or as directed by a doctor

Children under 2 years as a doctor

Inactive Ingredients

Ammonia, glycerin, purified water

Purpose

Skin Protectant

Box artwork

Front of package

Primary label

Label on actual product